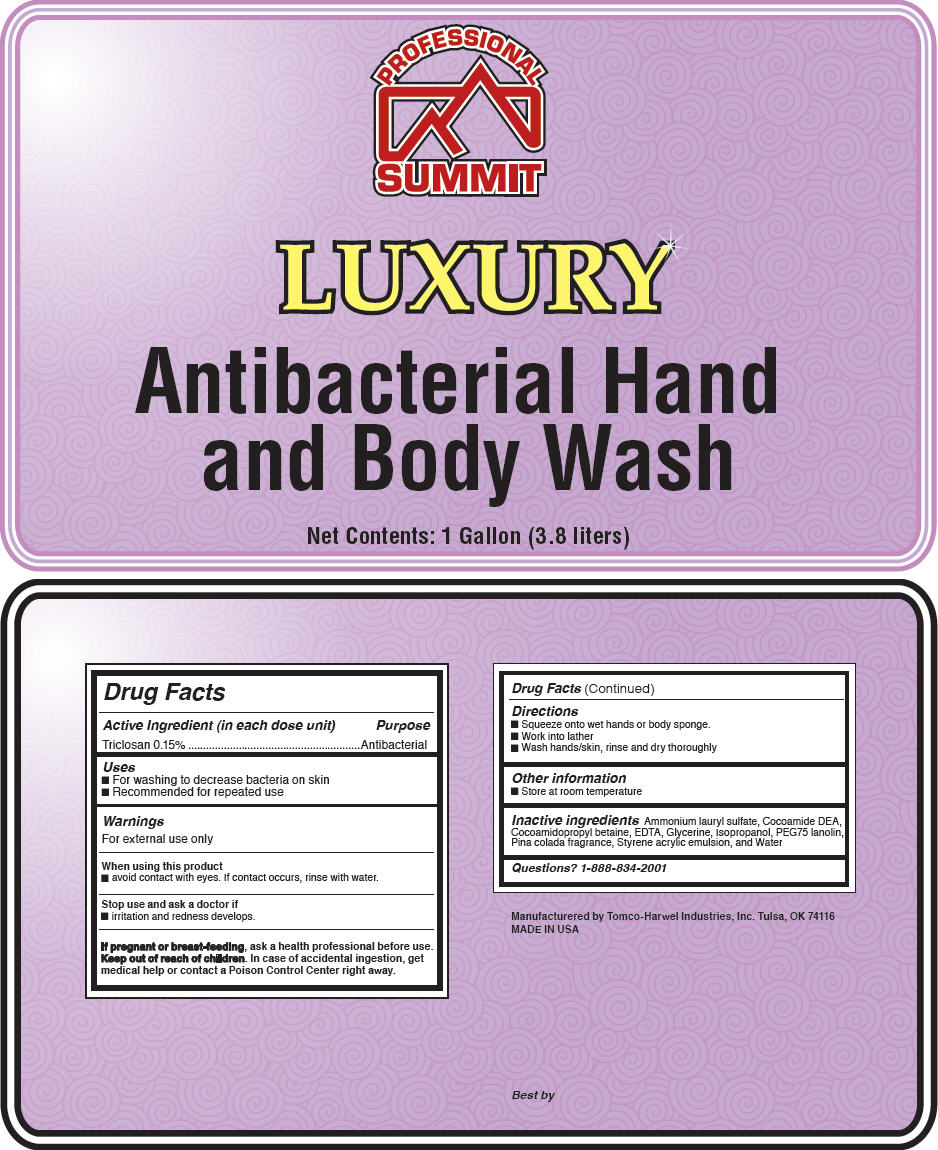 DRUG LABEL: Luxury
NDC: 60549-1129 | Form: LIQUID
Manufacturer: Tomco-Harwel Industries Inc
Category: otc | Type: HUMAN OTC DRUG LABEL
Date: 20140415

ACTIVE INGREDIENTS: Triclosan 1.5 g/1 L
INACTIVE INGREDIENTS: Water; EDETATE SODIUM; AMMONIUM LAURYL SULFATE; LANOLIN; GLYCERIN; ISOPROPYL ALCOHOL; COCAMIDOPROPYL BETAINE; COCO DIETHANOLAMIDE

Luxury

Drug Facts

Active Ingredient (in each dose unit)

Triclosan 0.15%

Purpose

Antibacterial

Uses

- For washing to decrease bacteria on skin
- Recommended for repeated use

Warnings

For external use only

When using this product

- avoid contact with eyes. If contact occurs, rinse with water.

Stop use and ask a doctor if

- irritation and redness develops.

PREGNANCY OR BREAST FEEDING

If pregnant or breast-feeding, ask a health professional before use.

Keep out of reach of children. In case of accidental ingestion, get medical help or contact a Poison Control Center right away.

Directions

- Squeeze onto wet hands or body sponge.
- Work into lather
- Wash hands/skin, rinse and dry thoroughly

Other information

- Store at room temperature

Inactive ingredients

Ammonium lauryl sulfate, Cocoamide DEA, Cocoamidopropyl betaine, EDTA, Glycerine, Isopropanol, PEG75 lanolin, Pina colada fragrance, Styrene acrylic emulsion, and Water

Questions?

1-888-834-2001

Manufacturered by Tomco-Harwel Industries, Inc. Tulsa, OK 74116

PRINCIPAL DISPLAY PANEL - 3.8 L Bottle Label

PROFESSIONAL
SUMMIT

LUXURY

Antibacterial Hand
and Body Wash

Net Contents: 1 Gallon (3.8 liters)